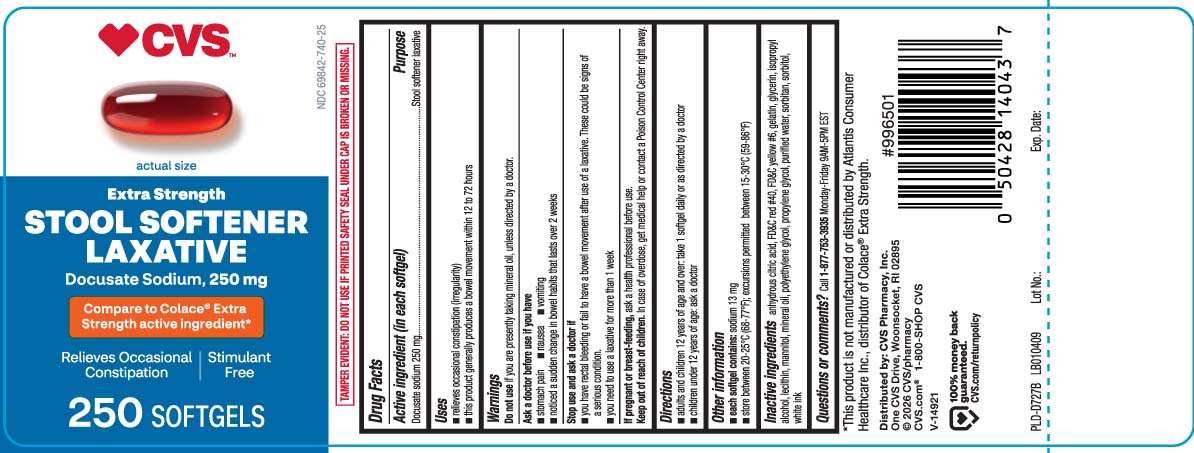 DRUG LABEL: Stool Softener
NDC: 69842-740 | Form: CAPSULE, LIQUID FILLED
Manufacturer: CVS Pharmacy
Category: otc | Type: HUMAN OTC DRUG LABEL
Date: 20251217

ACTIVE INGREDIENTS: DOCUSATE SODIUM 250 mg/1 1
INACTIVE INGREDIENTS: FD&C RED NO. 40; FD&C YELLOW NO. 6; GELATIN; GLYCERIN; POLYETHYLENE GLYCOL, UNSPECIFIED; PROPYLENE GLYCOL; WATER; SORBITOL

Drug Facts

Active ingredient (in each softgel)

Docusate sodium 250 mg

Purpose

Stool softener laxative

Uses

- for relief of occasional constipation
- this product generally produces a bowel movement within 12 to 72 hours

Warnings

Do not use

if you are presently taking mineral oil, unless directed by a doctor.

Ask a doctor before use if you have

- stomach pain
- nausea
- vomiting
- noticed a sudden change in bowel habits that last over 2 weeks

Stop use and ask a doctor if

- you have rectal bleeding or fail to have a bowel movement after use of a laxative. These could be signs of a serious condition.
- you need to use a laxative for more than 1 week

If pregnant or breast-feeding

ask a health professional before use.

Keep out of reach of children.

In case of overdose, get medical help or contact a Poison Control Center right away.

Directions

- adults and children 12 years of age and over: take 1 softgel daily or as directed by a doctor
- children under 12 years of age: ask a doctor

Other information

- each softgel contains: sodium 15 mg
- store between 20-25ºC(68-77ºF); excursions permitted between 15-30ºC (59-86ºF)

Inactive Ingredients

edible white ink, FD&C red #40, FD&C yellow #6, gelatin, glycerin, mannitol, polyethylene glycol, propylene glycol, purified water, sorbitan, sorbitol

Questions or comments?

Call 1-877-753-3935 Monday- Friday 9AM-5PM EST

Principal Display Panel

Compare to Colace® Extra Strength active ingredient*

Extra Strength

STOOL SOFTENER LAXATIVE

Docusate Sodium, 250 mg

Relieves Occasional Constipation

Stimulant Free

SOFTGELS

*This product is not manufactured or distributed by Atlantis Consumer Healthcare Inc., distributor of Colace® Extra Strength.

TAMPER EVIDENT: DO NOT USE IF PRINTED SAFETY SEAL UNDER CAP IS BROKEN OR MISSING.

Distributed by:

CVS Pharmacy, Inc.

One CVS Drive

Woonsocket, RI 02895

Product Label

CVS Extra Strength Stool Softener Laxative